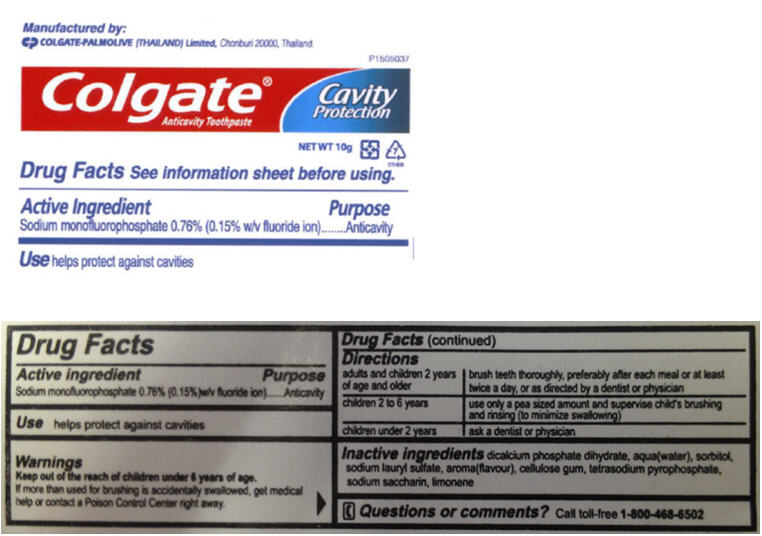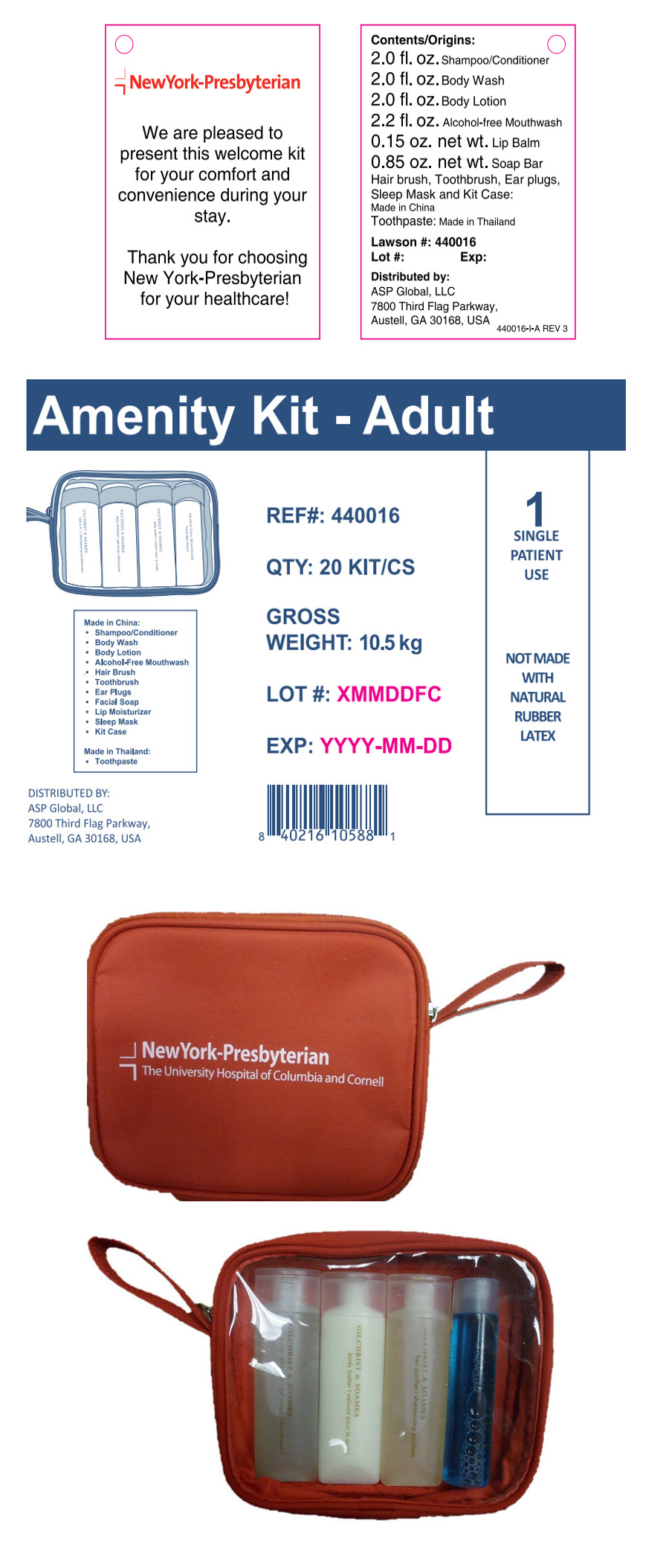 DRUG LABEL: NewYork-Presbyterian Amenity
NDC: 59448-100 | Form: KIT | Route: DENTAL
Manufacturer: ASP Global, LLc
Category: otc | Type: HUMAN OTC DRUG LABEL
Date: 20241217

ACTIVE INGREDIENTS: Sodium Monofluorophosphate 7.6 mg/1 g
INACTIVE INGREDIENTS: Dibasic Calcium Phosphate Dihydrate; Water; Sorbitol; Sodium Lauryl Sulfate; Sodium Pyrophosphate; Saccharin Sodium

NewYork-Presbyterian

Colgate® Anticavity Toothpaste

Drug Facts

Active ingredient

Sodium monofluorophosphate 0.76% (0.15% w/v fluoride ion)

Purpose

Anticavity

Use

helps protect against cavities

Warnings

KEEP OUT OF REACH OF CHILDREN

Keep out of the reach of children under 6 years of age. If more than used for brushing is accidentally swallowed, get medical help or contact a Poison Control Center right away.

Directions

adults and children 2 years of age and older | brush teeth thoroughly, preferably after each meal or at least twice a day, or as directed by a dentist or physician
children 2 to 6 years | use only a pea sized amount and supervise child's brushing and rinsing (to minimize swallowing)
children under 2 years | ask a dentist or physician

Inactive ingredients

dicalcium phosphate dihydrate, water, sorbitol, sodium lauryl sulfate, flavor, cellulose gum, tetrasodium pyrophosphate, sodium saccharin

Questions or comments?

Call toll-free 1-800-468-6502

PRINCIPAL DISPLAY PANEL - 10 g Tube Label

Colgate®
Anticavity Toothpaste

Cavity
Protection

PRINCIPAL DISPLAY PANEL - Amenity Kit

NewYork-Presbyterian

We are pleased to
present this welcome kit
for your comfort and
convenience during your
stay.

Thank you for choosing
New York-Presbyterian
for your healthcare!

Contents/Origins:
2.0 fl. oz. Shampoo/Conditioner
2.0 fl. oz. Body Wash
2.0 fl. oz. Body Lotion
2.2 fl. oz. Alcohol-free Mouthwash
0.15 oz. net wt. Lip Balm
0.85 oz. net wt. Soap Bar
Hair brush, Toothbrush, Ear plugs,
Sleep Mask and Kit Case:
Made in China
Toothpaste: Made in Thailand

Lawson #: 440016
Lot #:
Exp:

Distributed by:
ASP Global, LLC
7800 Third Flag Parkway,
Austell, GA 30168, USA

440016-I-A REV 3

Amenity Kit - Adult

Made in China:

- Shampoo/Conditioner
- Body Wash
- Body Lotion
- Alcohol-Free Mouthwash
- Hair Brush
- Toothbrush
- Ear Plugs
- Facial Soap
- Lip Moisturizer
- Sleep Mask
- Kit Case

Made in Thailand:

- Toothpaste

REF#: 440016

QTY: 20 KIT/CS

GROSS
WEIGHT: 10.5 kg

LOT #: XMMDDFC

EXP: YYYY-MM-DD

1
SINGLE
PATIENT
USE

NOT MADE
WITH
NATURAL
RUBBER
LATEX

DISTRIBUTED BY:
ASP Global, LLC
7800 Third Flag Parkway,
Austell, GA 30168, USA

NewYork-Presbyterian
The University Hospital of Columbia and Cornell